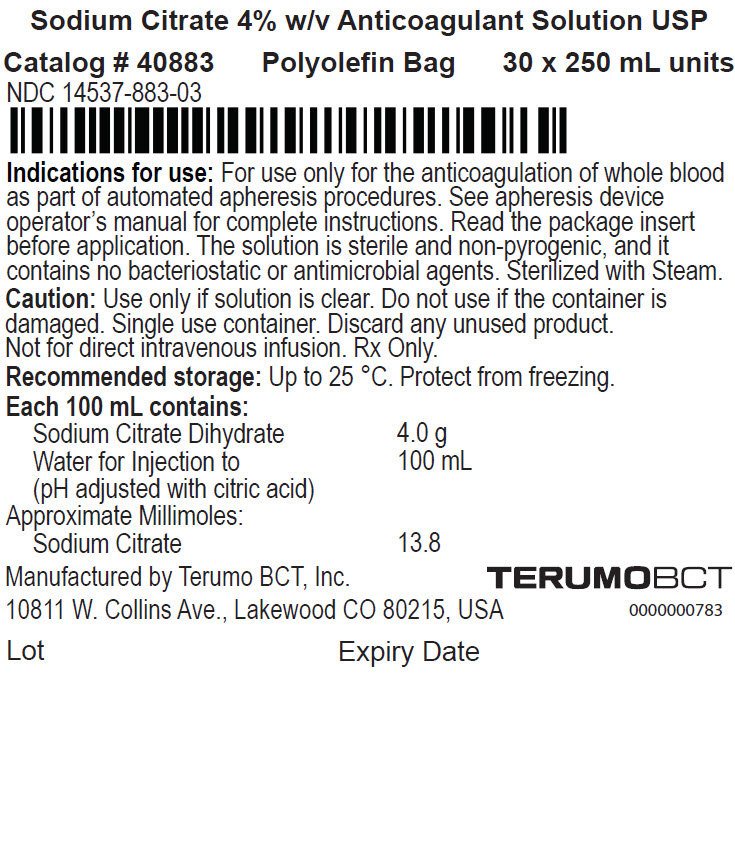 DRUG LABEL: Sodium Citrate w/v Anticoagulant
NDC: 14537-883 | Form: INJECTION, SOLUTION
Manufacturer: Terumo BCT, Ltd
Category: prescription | Type: HUMAN PRESCRIPTION DRUG LABEL
Date: 20250124

ACTIVE INGREDIENTS: TRISODIUM CITRATE DIHYDRATE 4 g/100 mL
INACTIVE INGREDIENTS: water; Citric Acid monohydrate

HIGHLIGHTS OF PRESCRIBING INFORMATION

These highlights do not include all the information needed to use SODIUM CITRATE 4% W/V ANTICOAGULANT SOLUTION USP safely and effectively. See full prescribing information for SODIUM CITRATE 4% W/V ANTICOAGULANT SOLUTION USP.
SODIUM CITRATE 4% W/V ANTICOAGULANT SOLUTION USP
Sterile Fluid
Polyolefin Bag
Initial U.S. Approval: 1978

1 INDICATIONS AND USAGE

SODIUM CITRATE 4% W/V ANTICOAGULANT SOLUTION USP is intended for use only for the anticoagulation of whole blood as part of automated apheresis procedures. (1)

2 DOSAGE AND ADMINISTRATION

- SODIUM CITRATE 4% W/V ANTICOAGULANT SOLUTION USP is added to tubing sets during apheresis procedures. (2)
- SODIUM CITRATE 4% W/V ANTICOAGULANT SOLUTION USP may only be used with apheresis devices. For instructions on the use of the solution see the apheresis device operator's manual. (2.1)
- Follow the directions for connecting the SODIUM CITRATE 4% W/V ANTICOAGULANT SOLUTION USP bag to the apheresis system. (2.2)

3 DOSAGE FORMS AND STRENGTHS

- 250 mL sterile fluid in a polyolefin bag. (3)

4 CONTRAINDICATIONS

- DO NOT INFUSE SODIUM CITRATE 4% W/V ANTICOAGULANT SOLUTION USP DIRECTLY TO THE DONOR. (4)

5 WARNINGS AND PRECAUTIONS

- Verify that the SODIUM CITRATE 4% W/V ANTICOAGULANT SOLUTION USP has been securely attached to the anticoagulant (AC) line on the system tubing set. Use aseptic technique throughout all procedures to ensure donor safety and quality.
- Single-use container, do not reuse. Discard any unused or partially used product.
- Rx only (5)

6 ADVERSE REACTIONS

Citrate reactions or toxicity may occur with the infusion and return of blood containing citrate anticoagulant. The recipient of the blood containing citrate should be monitored for the signs and symptoms of citrate toxicity. (6)

To report SUSPECTED ADVERSE REACTIONS, contact Terumo BCT, Inc. at 1-877-339-4228 or FDA at 1-800-FDA-1088 or www.fda.gov/medwatch.

8 USE IN SPECIFIC POPULATIONS

SODIUM CITRATE 4% W/V ANTICOAGULANT SOLUTION USP has not been studied in controlled clinical trials with specific populations.

FULL PRESCRIBING INFORMATION

1 INDICATIONS AND USAGE

SODIUM CITRATE 4% W/V ANTICOAGULANT SOLUTION USP is intended for use only for the anticoagulation of whole blood as part of automated apheresis procedures. [See Dosage and Administration (2).]

2 DOSAGE AND ADMINISTRATION

2.1 General Dosing Information

SODIUM CITRATE 4% W/V ANTICOAGULANT SOLUTION USP is added to tubing sets during apheresis procedures. The solution bag is connected to the tubing set in an apheresis collection. The recommended dose is determined by the apheresis device and metered into the tubing set by the apheresis device. It is not intended for direct intravenous infusion.

For instructions on the use of the solution with the apheresis device and tubing set, see the device operator's manual.

2.2 Administration

- Ensure solution is the SODIUM CITRATE 4% W/V ANTICOAGULANT SOLUTION USP and is within the expiration date.
- Inspect the bag. Do not use if the container is damaged, leaking or if there is any visible sign of deterioration.
- Use only if solution is clear and free of particulate matter.
- Protect from sharp objects.

Directions for connecting the SODIUM CITRATE 4% W/V ANTICOAGULANT SOLUTION USP bag to the apheresis device.

At the prompt to connect anticoagulant to the apheresis device tubing set:

1. Remove the overwrap by pulling down at the notch, and remove the SODIUM CITRATE 4% W/V ANTICOAGULANT SOLUTION USP bag.
2. Before use, perform the following checks [see Warnings and Precautions (5)]:
  - Check for leaks by gently squeezing the bag. If leaks are found, discard the bag.
  - Ensure that the solution is the SODIUM CITRATE 4% W/V ANTICOAGULANT SOLUTION USP and is within the expiration date.
  - Inspect the solution in good light. Bags showing cloudiness, haze, or particulate matter should not be used.
3. Remove the protective cap from the port on the bag.
4. Connect the bag to the apheresis device tubing set using aseptic technique and hang the solution.
5. Proceed according to the apheresis device operator's manual.

Parenteral drug products should be inspected visually for particulate matter and discoloration prior to administration, whenever the solution and container permit.

3 DOSAGE FORMS AND STRENGTHS

250 mL SODIUM CITRATE 4% W/V ANTICOAGULANT SOLUTION USP is a sterile solution in a polyolefin bag. Each 100 mL contains: Sodium Citrate (dihydrate) 4.0 g; Water for Injection to 100 mL, (pH adjusted with citric acid). Approximate millimoles of Sodium Citrate: 13.8.

4 CONTRAINDICATIONS

DO NOT INFUSE SODIUM CITRATE 4% W/V ANTICOAGULANT SOLUTION USP DIRECTLY TO THE DONOR.

5 WARNINGS AND PRECAUTIONS

- Verify that the SODIUM CITRATE 4% W/V ANTICOAGULANT SOLUTION USP has been securely attached to the anticoagulant (AC) line on the system tubing set. Use aseptic technique throughout all procedures to ensure donor safety and quality.
- Single-use container. Do not reuse. Discard any unused or partially used product.
- Rx only.

6 ADVERSE REACTIONS

Citrate reactions or toxicity may occur with the infusion of blood products to patients and return of blood containing citrate anticoagulant to donors. The recipient of the blood containing citrate should be monitored for the signs and symptoms of citrate toxicity. The signs and symptoms of citrate toxicity begin with paresthesia, a "tingling" sensation around the mouth or in the extremities, followed by severe reactions that are characterized by hypotension and possible cardiac arrhythmia. Citrate toxicity may occur more frequently in patients who are hypothermic, have impaired liver or renal function, or have low calcium levels because of an underlying disease.

8 USE IN SPECIFIC POPULATIONS

SODIUM CITRATE 4% W/V ANTICOAGULANT SOLUTION USP has not been adequately studied in controlled clinical trials with specific populations.

11 DESCRIPTION

SODIUM CITRATE 4% W/V ANTICOAGULANT SOLUTION USP is designed to be metered by an apheresis device in apheresis procedures, to prevent platelet activation and coagulation as blood moves throughout the extracorporeal unit (tubing set) in an apheresis procedure.

The solution is sterile and non-pyrogenic, and it contains no bacteriostatic or antimicrobial agents. Sterilized with steam.

The formulas of the active ingredients are provided in Table 1.

Table 1: Active Ingredients
Ingredients | Molecular Formula | Molecular Weight
Sodium Citrate Dihydrate | C6H9Na3O9 | 294.10
Water for Injection | H2O | 18.00

Each 100 mL of SODIUM CITRATE 4% W/V ANTICOAGULANT SOLUTION USP contains: Sodium Citrate (dihydrate) 4.0 g; and Water for Injection to 100 mL (pH adjusted with citric acid). Approximate millimoles of sodium citrate: 13.8.

The polyolefin bag is not made with natural rubber latex.

The bag contains materials that have been tested to demonstrate the suitability of the container for storing pharmaceutical solutions. The bag is nontoxic and biologically inert. The bag-solution unit is a closed system and is not dependent upon entry of external air during administration. The bag is overwrapped to provide protection from the physical environment and to provide an additional moisture barrier when necessary.

12 CLINICAL PHARMACOLOGY

12.1 Mechanism of Action

SODIUM CITRATE 4% W/V ANTICOAGULANT SOLUTION USP acts as an extracorporeal anticoagulant by binding the free calcium in the blood. Calcium is a necessary co-factor to several steps in the clotting cascade. The following ingredients are key components of the solution:

- Citric acid for pH regulation
- Sodium Citrate anticoagulant

This solution has no pharmacological effect.

16 HOW SUPPLIED/STORAGE AND HANDLING

SODIUM CITRATE 4% W/V ANTICOAGULANT SOLUTION USP is a clear solution supplied in sterile and non-pyrogenic polyolefin bags. The bags are packaged 30 bags per case.

SIZE | CATALOG NUMBER | NDC NUMBER
250 mL | 40883 | Bag: | 14537-883-00
 |  | Case: | 14537-883-03

STORAGE

Up to 25 °C.

Protect from freezing.

Issued: December 2019

Manufactured by
Terumo BCT, Inc.
10811 W. Collins Ave.
Lakewood, CO 80215

PRINCIPAL DISPLAY PANEL - 250 mL Bag Carton Label

Sodium Citrate 4% w/v Anticoagulant Solution USP

Catalog # 40883
Polyolefin Bag
30 x 250 mL units

NDC 14537-883-03

Indications for use: For use only for the anticoagulation of whole blood
as part of automated apheresis procedures. See apheresis device
operator's manual for complete instructions. Read the package insert
before application. The solution is sterile and non-pyrogenic, and it
contains no bacteriostatic or antimicrobial agents. Sterilized with Steam.

Caution: Use only if solution is clear. Do not use if the container is
damaged. Single use container. Discard any unused product.
Not for direct intravenous infusion. Rx Only.

Recommended storage: Up to 25 °C. Protect from freezing.

Each 100 mL contains:
Sodium Citrate Dihydrate
4.0 g
Water for Injection to
(pH adjusted with citric acid)
100 mL
Approximate Millimoles:
Sodium Citrate
13.8

Manufactured by Terumo BCT, Inc.
10811 W. Collins Ave., Lakewood CO 80215, USA

TERUMOBCT
0000000783

Lot
Expiry Date